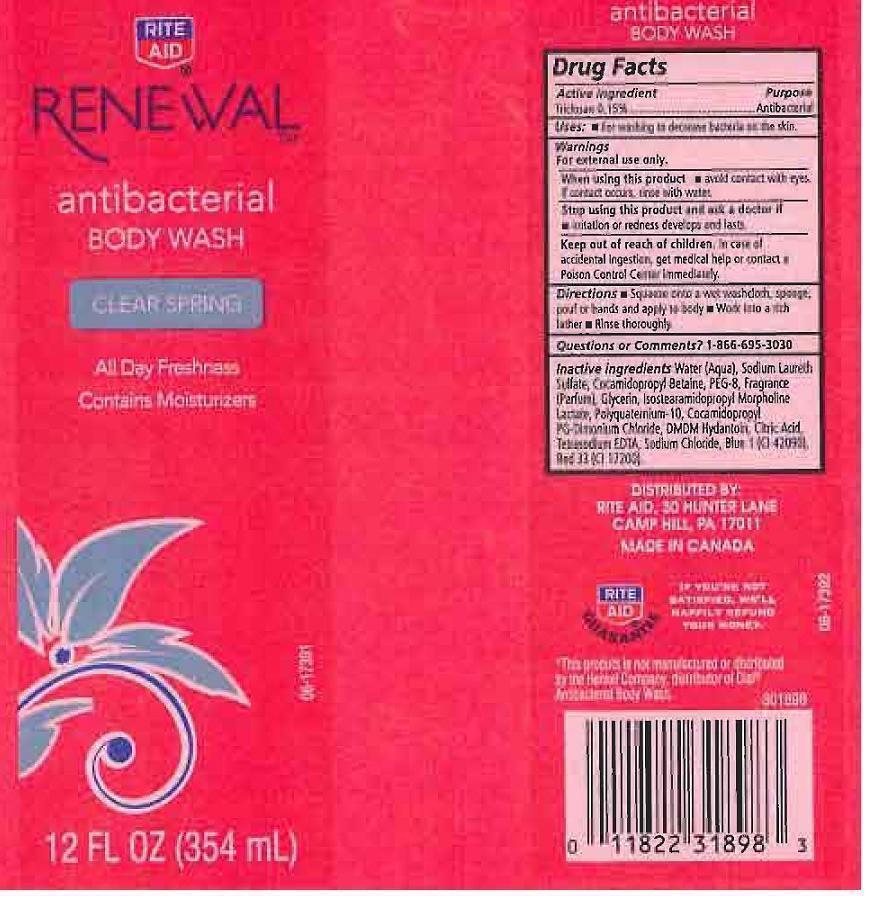 DRUG LABEL: RITE AID RENEWAL
NDC: 11822-8010 | Form: LIQUID
Manufacturer: RITE AID CORPORATION
Category: otc | Type: HUMAN OTC DRUG LABEL
Date: 20120925

ACTIVE INGREDIENTS: TRICLOSAN 1.5 mg/1 mL
INACTIVE INGREDIENTS: WATER; SODIUM LAURETH SULFATE; COCAMIDOPROPYL BETAINE; POLYETHYLENE GLYCOL 400; GLYCERIN; ISOSTEARAMIDOPROPYL MORPHOLINE LACTATE; POLYQUATERNIUM-10 (400 CPS AT 2%); COCAMIDOPROPYL PG-DIMONIUM CHLORIDE; DMDM HYDANTOIN; CITRIC ACID MONOHYDRATE; EDETATE SODIUM; SODIUM CHLORIDE; FD&C BLUE NO. 1; D&C RED NO. 33

DRUG FACTS

ACTIVE INGREDIENT

TRICLOSAN 0.15%

PURPOSE

ANTIBACTERIAL

USES

FOR WASHING TO DECREASE BACTERIA ON THE SKIN.

WARNINGS

FOR EXTERNAL USE ONLY.

WHEN USING THIS PRODUCT

STOP USING THIS PRODUCT AND ASK A DOCTOR IF

KEEP OUT OF REACH OF CHILDREN

IN CASE OF ACCIDENTAL INGESTION, GET MEDICAL HELP OR CONTACT A POISON CONTROL CENTER IMMEDIATELY.

DIRECTIONS

SQUEEZE ONTO A WET WASHCLOTH, SPONGE, POUF OR HANDS AND APPLY TO BODY. WORK INTO A RICH LATHER. RINSE THOROUGHLY.

QUESTIONS OR COMMENTS?

1-866-695-3030

INACTIVE INGREDIENTS

WATER (AQUA), SODIUM LAURETH SULFATE, COCAMIDOPROPYL BETAINE, PEG-8, FRAGRANCE (PARFUM), GLYCERIN, ISOSTEARAMIDOPROPYL MORPHOLINE LACTATE, POLYQUATERNIUM-10, COCAMIDOPROPYL PG-DIMONIUM CHLORIDE, DMDM HYDANTOIN, CITRIC ACID, TETRASODIUM EDTA, SODIUM CHLORIDE, BLUE 1 (CI 42090), RED 33 (CI 17200).